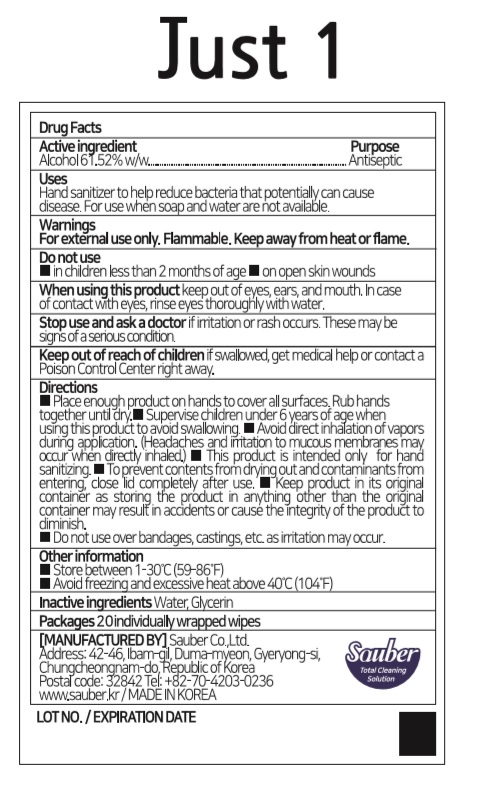 DRUG LABEL: Just 1
NDC: 78880-062 | Form: CLOTH
Manufacturer: Sauber Co.,Ltd.
Category: otc | Type: HUMAN OTC DRUG LABEL
Date: 20200710

ACTIVE INGREDIENTS: ALCOHOL 0.6152 1/1 1
INACTIVE INGREDIENTS: WATER; GLYCERIN

Just 1 | 20 ct. in 1 BOX | 78880-062-20 | HAND SANITIZING WIPES